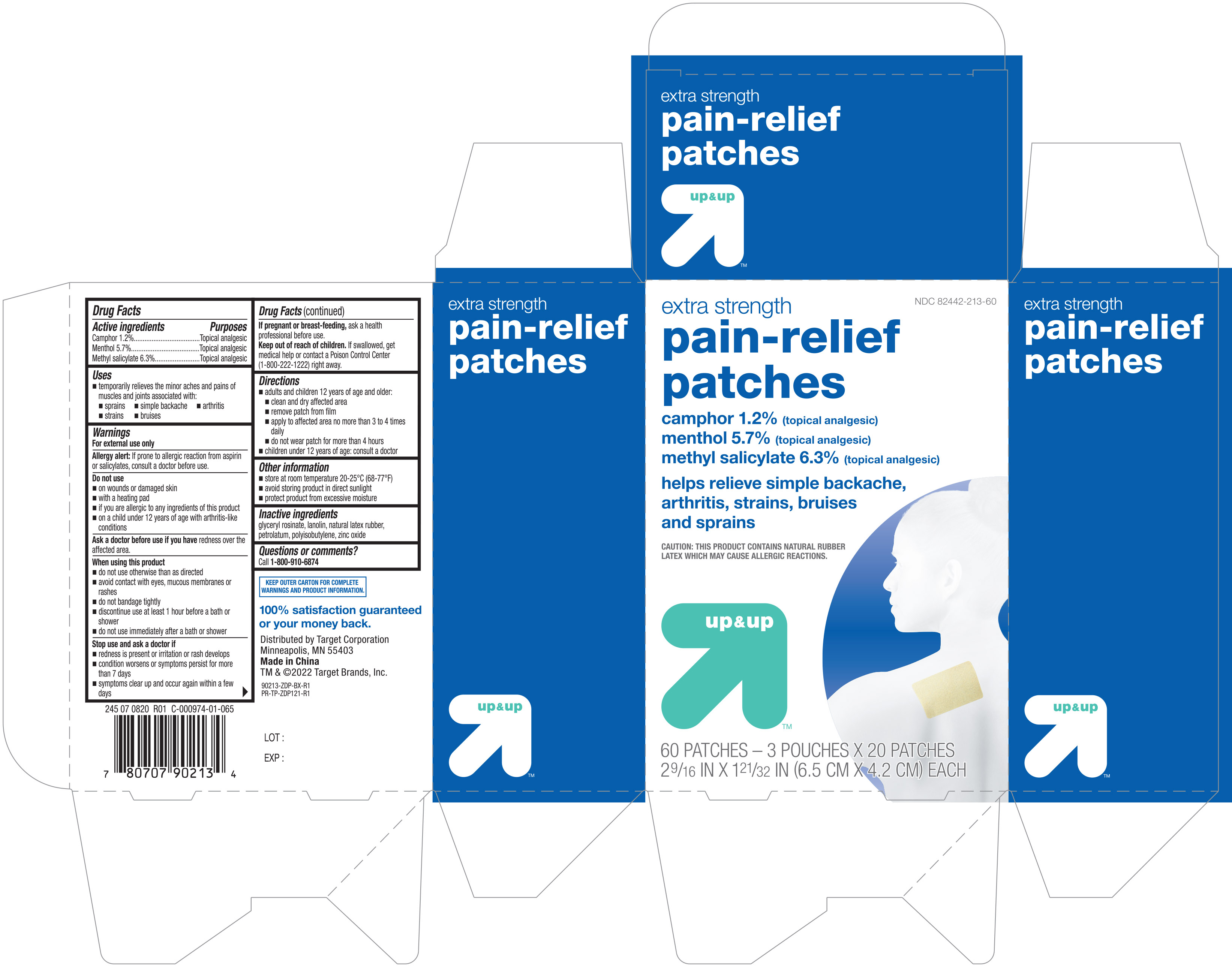 DRUG LABEL: Up and Up Pain
NDC: 82442-213 | Form: PATCH
Manufacturer: Target Corporation
Category: otc | Type: HUMAN OTC DRUG LABEL
Date: 20241220

ACTIVE INGREDIENTS: CAMPHOR (SYNTHETIC) 12 mg/1 1; MENTHOL 57 mg/1 1; METHYL SALICYLATE 63 mg/1 1
INACTIVE INGREDIENTS: NATURAL LATEX RUBBER; ZINC OXIDE; GLYCERYL ROSINATE; LANOLIN; PETROLATUM; POLYISOBUTYLENE (1000 MW)

Active ingredients Purposes

Camphor 1.2%....................................................Topical analgesic

Menthol 5.7%......................................................Topical analgesic

Methyl Salicylate 6.3%........................................Topical analgesic

Uses

temporarily relieves the minor aches and pains of muscles and joints associated with:

- sprains
- simple backache
- arthirtis
- strains
- bruises

Warnings

For external use only

Allergy alert: If prone to allergic reaction from aspirin or salicylates, consult a doctor before use

Do not use

- on wounds or damaged skin
- with a heating pad
- if you are allergic to any ingredients of this product
- on a child under 12 years of age with arthritis-like conditions

Ask a doctor before use if you have redness over the affected area

When using this product

- do not use otherwise than as directed
- avoid contact with eyes, mucous membranes or rashes
- do not bandage tightly
- discontinue use at least 1 hour before a bath or shower
- do not use immediately after a bath or shower

Stop use and ask a doctor if

- redness is present or irritation or rash develops
- condition worsens or symptoms persist for more than 7 days
- symptoms clear up and occur again within a few days

PREGNANCY OR BREAST FEEDING

If pregnant or breast-feeding, ask a health professional before use

Keep out of reach of children. If swallowed, get medical help or contact a Poison Control Center (1-800-222-1222) right away

Directions

- adults and children 12 years of age and older:
- clean and dry affected area
- remove patch from film
- apply to affected area no more than 3 to 4 times daily
- do not wear patch for more than 4 hours
- children under 12 years of age: consult a doctor

Other information

- store at room temperature 20-25°C (68-77°F)
- avoid storing product in direct sunlight
- protect product from excessive moisture

Inactive ingredients

glyceryl rosinate, lanolin, natural latex rubber, petrolatum, polyisobutylene, zinc oxide

DOSAGE AND ADMINISTRATION

Distributed by:

Target Corproation

Minneapolis, MN 55403

Made in China